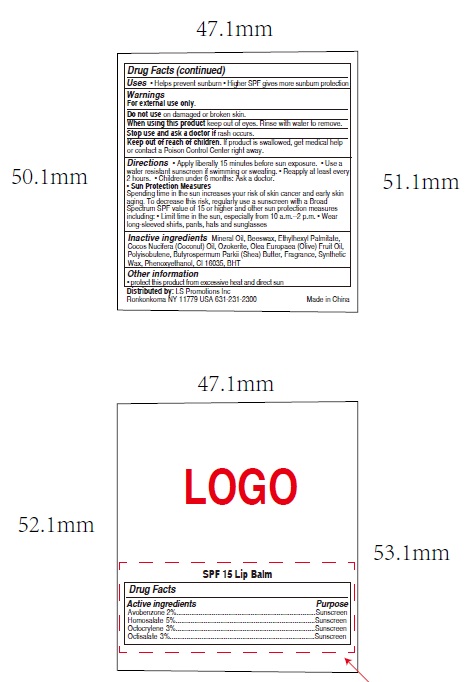 DRUG LABEL: Lip Balm SPF15 Bubble Gum Flavored
NDC: 72449-303 | Form: LIPSTICK
Manufacturer: LS Promotions Inc
Category: otc | Type: HUMAN OTC DRUG LABEL
Date: 20250327

ACTIVE INGREDIENTS: OCTOCRYLENE 3 g/100 g; HOMOSALATE 5 g/100 g; AVOBENZONE 2 g/100 g; OCTISALATE 3 g/100 g
INACTIVE INGREDIENTS: POLYISOBUTYLENE (1000 MW); PHENOXYETHANOL; BUTYROSPERMUM PARKII (SHEA) BUTTER; ETHYLHEXYL PALMITATE; SYNTHETIC WAX (1800 MW); FRAGRANCE 13576; OLEA EUROPAEA (OLIVE) FRUIT OIL; MINERAL OIL; CERESIN; FD&C RED NO. 40; BHT; BEESWAX; COCOS NUCIFERA (COCONUT) OIL

Lip Balm SPF15 Bubble Gum Flavored

Drug Facts

Active Ingredients

Octocrylene 3%

Homosalate 5%

Avobenzone 2%

Octisalate 3%

Purpose

Sunscreen

Uses

Helps prevent sunburn

Warnings

For external use only

Do not Use on Damaged or Broken Skin

Stop Use and Ask a Doctor

if rash occurs

When using this product

keep out of eyes. Rinse with water to remove.

Keep out of reach of children

If swallowed, get medical help or

contact a Poison Control Center right away

Directions

▪ Apply liberally 15 minutes before sun exposure

▪ Reapply at least every 2 hours

▪ Use a water resistant sunscreen if swimming or sweating

▪Children under 6 months of age: Ask a doctor

Sun Protection Measures

Spending time in the sun increases your risk

of skin cancer and early skin aging. To decrease this risk, regularly use a

sunscreen with a Broad Spectrum SPF value of 15 or higher and other sun

protection measures including: ▪Limit time in the sun, especially from

10am to 2 pm ▪ Wear long sleeved shirts, pants, hats, and sunglasses

Inactive Ingredients

Mineral oil, beeswax, ethylhexyl palmitate,

ozokerite, cocos nucifera (coconut) oil, olea europaea (olive) fruit oil,

polyisobutene, butyrospermum parkii (shea) butter, synthetic wax,

fragrance, phenoxyethanol, Red 40, BHT.

Questions or Comments?

Call weekdays from 9AM to 5PM EST

at 631-231-2300

Package Label PDP

Lip Balm SPF15 Bubble Gum Flavored (NDC 72449-303-01)